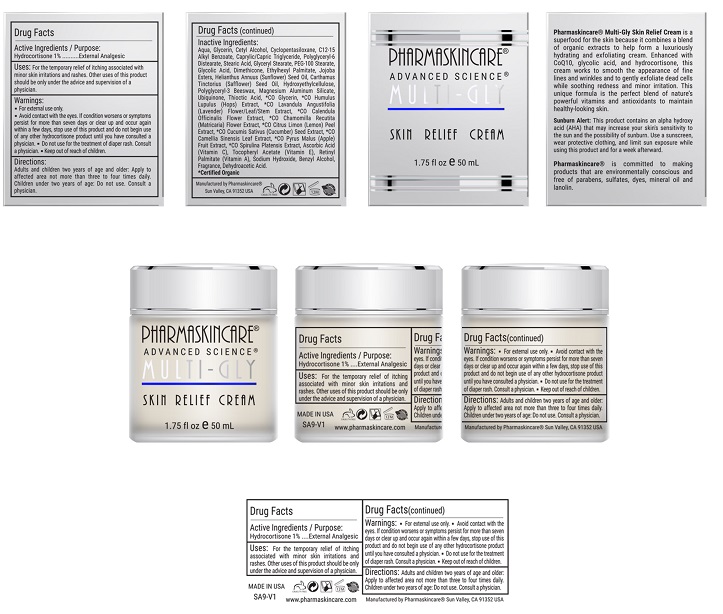 DRUG LABEL: Pharmaskincare Multi-Gly Skin Relief Cream
NDC: 68062-9106 | Form: LOTION
Manufacturer: Spa de Soleil
Category: otc | Type: HUMAN OTC DRUG LABEL
Date: 20171011

ACTIVE INGREDIENTS: HYDROCORTISONE 0.025 mg/2.5 mL
INACTIVE INGREDIENTS: MEDIUM-CHAIN TRIGLYCERIDES; WATER; CETYL ALCOHOL; ALKYL (C12-15) BENZOATE; CYCLOMETHICONE 5

Pharmaskincare Multi-Gly Skin Relief Cream

Active Ingredient

Hydrocortisone 1%

Purpose

External Analgesic

Warnings

- For external use only.
- Avoid contact with the eyes
- If condition worsens or symptoms persist for more than seven days or clear up and occur again within a few days, stope use of this product and do not begin use of any hydrocortisone product until you have consulted a physician.
- Do not use for the treatment of diaper rash. Consult a physician.
- Keep out of reach of children.

Directions

Adults and children two years of age and older: Apply to affected area not more than three or four times daily. Children under two years of age: Do not use; consult a physician.

Uses:

For the temporary relief of itching associated with minor skin irritations and rashes. Other uses of this product should be only under the advice and supervision of a physician.

Inactive Ingredients:

Water, Glycerin, Cetyl Alcohol, Cyclopentasiloxane, C12-15 Alkyl Benzoate, Caprylic/Capric Triglyceride, Stearic Acid, PEG-100 Stearate, Glyceryl Stearate, Glycolic Acid, Polyacrylamide, C13-14 Isoparaffin, Laureth-7, Dimethicone, Ethylhexyl Palmitate, Polyglyceryl-3 Beeswax, Polyglyceryl-6 Distearate, Jojoba Esters, Helianthus Annuus (Sunflower) Seed Oil, Carthamus Tinctorius (Safflower) Seed Oil, Hydroxyethylcellulose, Magnesium Aluminum Silicate, Thioctic Acid, Ubiquinone, *CO Glycerin, Malus Domestica Fruit Cell Culture Extract, *CO Humulus Lupulus (Hops) Extract, *CO Lavandula Angustifolia (Lavender) Flower/Leaf/Stem Extract, *CO Calendula Officinalis Flower Extract, *CO Chamomilla Recutita (Matricaria) Flower Extract, *CO Citrus Limon (Lemon) Peel Extract, *CO Cucumis Sativus (Cucumber) Seed Extract, *CO Camellia Sinensis Leaf Extract, *CO Pyrus Malus (Apple) Fruit Extract, *CO Spirulina Platensis Extract, Xanthan Gum, Lecithin, Ascorbic Acid (Vitamin C), Tocopheryl Acetate (Vitamin E), Retinyl Palmitate (Vitamin A), Sodium Hydroxide, Benzyl Alcohol, Fragrance, Dehydroacetic Acid

Warning

Keep out of reach of children.

PACKAGE LABEL

Pharmaskincare MultiGlySkinRelief.jpg